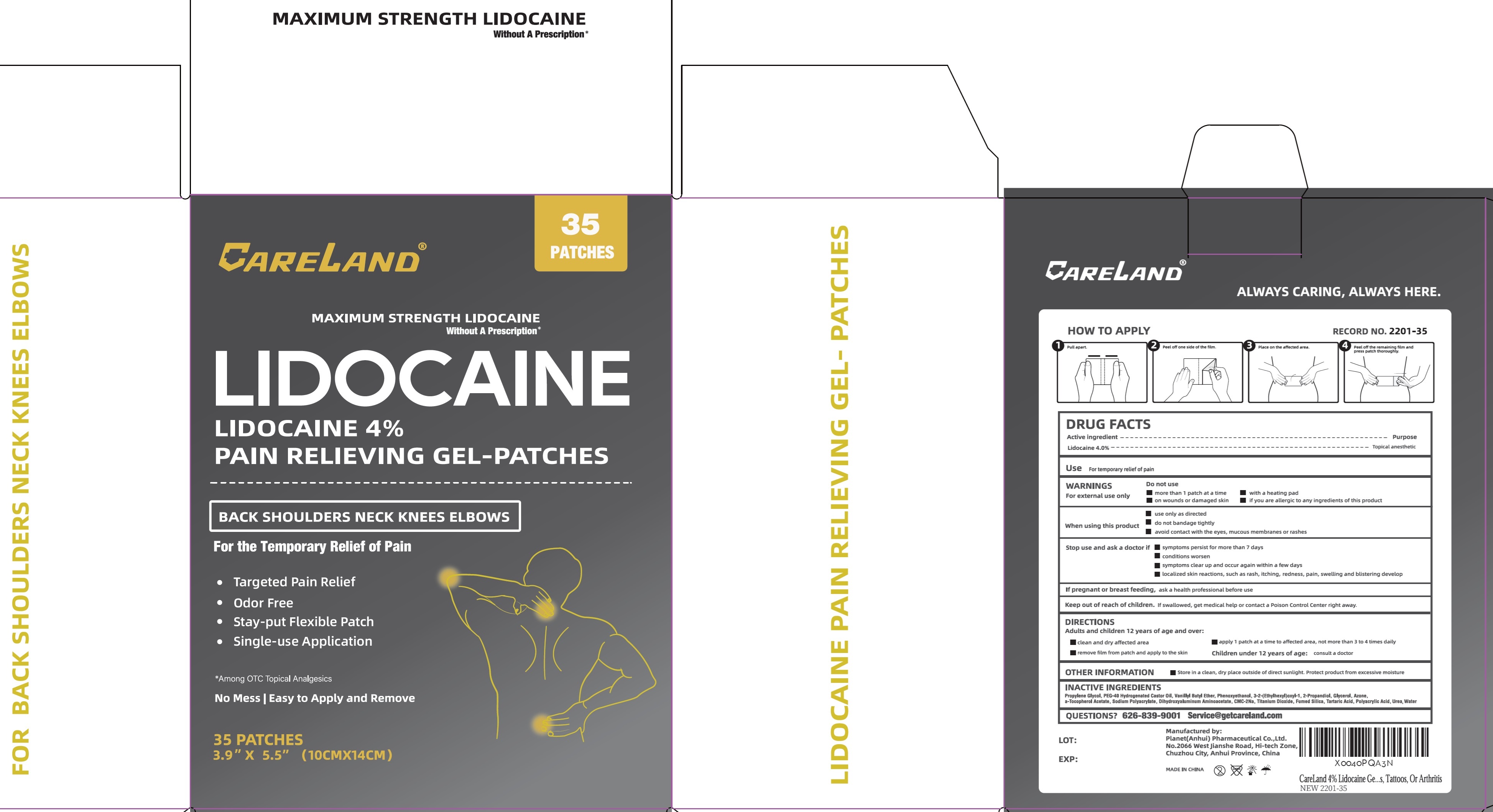 DRUG LABEL: Careland Lidocaine Pain Relieving
NDC: 75568-019 | Form: PATCH
Manufacturer: Planet (Anhui) Pharmaceutical Co., Ltd.
Category: otc | Type: HUMAN OTC DRUG LABEL
Date: 20260212

ACTIVE INGREDIENTS: LIDOCAINE 40 mg/1 g
INACTIVE INGREDIENTS: PROPYLENE GLYCOL; POLYOXYL 40 HYDROGENATED CASTOR OIL; VANILLYL BUTYL ETHER; PHENOXYETHANOL; GLYCERIN; LAUROCAPRAM; DIHYDROXYALUMINUM AMINOACETATE; TITANIUM DIOXIDE; TARTARIC ACID; UREA; WATER

Careland Lidocaine 4% Pain Relieving Gel Patches

Active ingredient

Lidocaine 4.0%

Purpose

Topical anesthetic

Use

For temporary relief of pain

WARNINGS

For external use only

Do not use

- more than 1 patch at a time
- on wounds or damaged skin
- with a heating pad
- if you are allergic to any ingredients of this product

When using this product

- use only as directed
- do not bandage tightly
- avoid contact with the eyes, mucous membranes or rashes

Stop use and ask a doctor if

- symptoms persist for more than 7 days
- conditions worsen
- symptoms clear up and occur again within a few days
- localized skin reactions, such as rash, itching, redness, pain, swelling and blistering develop

If pregnant or breast-feeding,

ask a health professional before use.

Keep out of reach of children.

If swallowed, get medical help or contact a Poison Control Center right away.

DIRECTIONS

Adults and children 12 years of age and over:

- clean and dry affected area
- remove film from patch and apply to the skin
- apply 1 patch at a time to affected area, not more than 3 to 4 times daily

Children under 12 years of age:consult a doctor

OTHER INFORMATION

- Store in a clean, dry place outside of direct sunlight. Protect product from excessive moisture

INACTIVE INGREDIENTS

Propylene Glycol, PEG-40 Hydrogenated Castor Oil, Vanillyl Butyl Ether, Phenoxyethanol, 3-2-(Ethylhexyl)oxyl-1, 2-Propandiol, Glycerol, Azone, a-Tocopherol Acetate, Sodium Polyacrylate, Dihydroxyaluminum Aminoacetate, CMC-2Na, Titanium Dioxide, Fumed Silica, Tartaric Acid, Polyacrylic Acid, Urea, Water

QUESTIONS?

626-839-9001 Service@getcareland.com